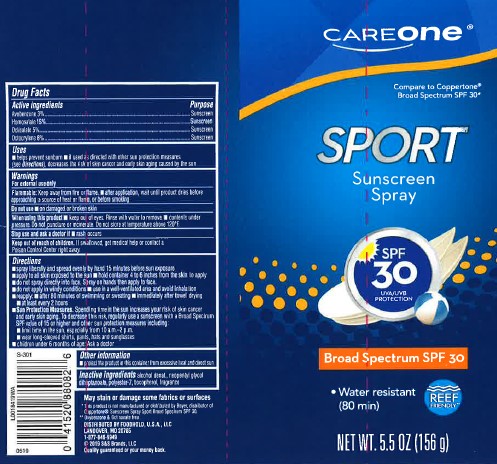 DRUG LABEL: Sunscreen
NDC: 72476-926 | Form: SPRAY
Manufacturer: Retail Business Services, LLC
Category: otc | Type: HUMAN OTC DRUG LABEL
Date: 20260206

ACTIVE INGREDIENTS: AVOBENZONE 3 g/100 g; HOMOSALATE 15 g/100 g; OCTISALATE 5 g/100 g; OCTOCRYLENE 8 g/100 g
INACTIVE INGREDIENTS: ALCOHOL; NEOPENTYL GLYCOL; NEOPENTYL GLYCOL DIHEPTANOATE; POLYESTER-7; TOCOPHEROL

Care One 926.000/926AA
Sport Sunscreen Spray SPF 30

Active ingredients

Avobenzone 3%

Homosalate 15%

Octisalate 5%

Octocrylene 8%

Purpose

sunscreen

Uses

- helps prevent sunburn
- if used as directed with other sun protection measures (see Directions), decreases the risk of skin cancer and early skin aging caused by the sun

Warnings

For external use only

Flammable:

Keep away from fire or flame.

- After application, wait until product dries before approaching a source of heat or flame, or before smoking

Do not use

on damaged or broken skin

When using this product

- keep out of eyes. Rinse with water to remove.
- contents under pressure. Do not puncture or incinerate. Do not store at temperature above 120° F.

Stop use and ask a doctor

rash occurs

Keep out of reach of children.

If swallowed, get medical help or contact a Poison Control Center right away.

Directions

- spray liberally and spread evenly by hand 15 minutes before sun exposure
- apply to all skin exposed to the sun
- hold container 4 to 6 inches from the skin to apply
- do not spray directly into face. Spray on hands then apply to face.
- do not apply in windy conditions
- use in a well-ventilated area and avoid inhalation
- reapply:
- after 80 minutes of swimming or sweating
- immediately after towel drying
- at least every 2 hours
- Sun Protection Measures.Spending time in the sun increases your risk of skin cancer and early skin aging. To decrease this risk, regularly use a sunscreen with a Broad Spectrum SPF value of 15 or higher and other sun protection measures including:
- limit time in the sun, especially from 10 a.m.–2 p.m.
- wear long-sleeved shirts, pants, hats and sunglasses
- children under 6 months of age: Ask a doctor

Other information

- protect the product in this container from excessive heat and direct sun

Inactive ingredients

alcohol denat., neopentyl glycol diheptanoate, polyester-7, tocopherol, fragrance

ADVERSE REACTION

May stain or damage som fabrics or surfaces

*This product is not manufactured or distributed by Bayer, distributer of Coppertone Suynscreen Spray Sport Broad Spectrum SPF 30.

**Oxybenzone & octinoxate free

DISTRIBUTED BY FOODHOLD, U.S.A., LLC

LANDOVER, MD 20785

1-877-846-9949

©2019 S & S Brands, LLC

Quality guaranteed or your money back

principal display panel

CAREONE®

Compare to Coppertone® Broad Spectrum SPF 30*

SPORT

Sunscreen Spray SPF 30

UVA/UVB PROTECTION

Broad Spectrum SPF 30

- Water resistant (80 min)

REEF FRIENDLY**

NET WT. 5.5 OZ (156 g)